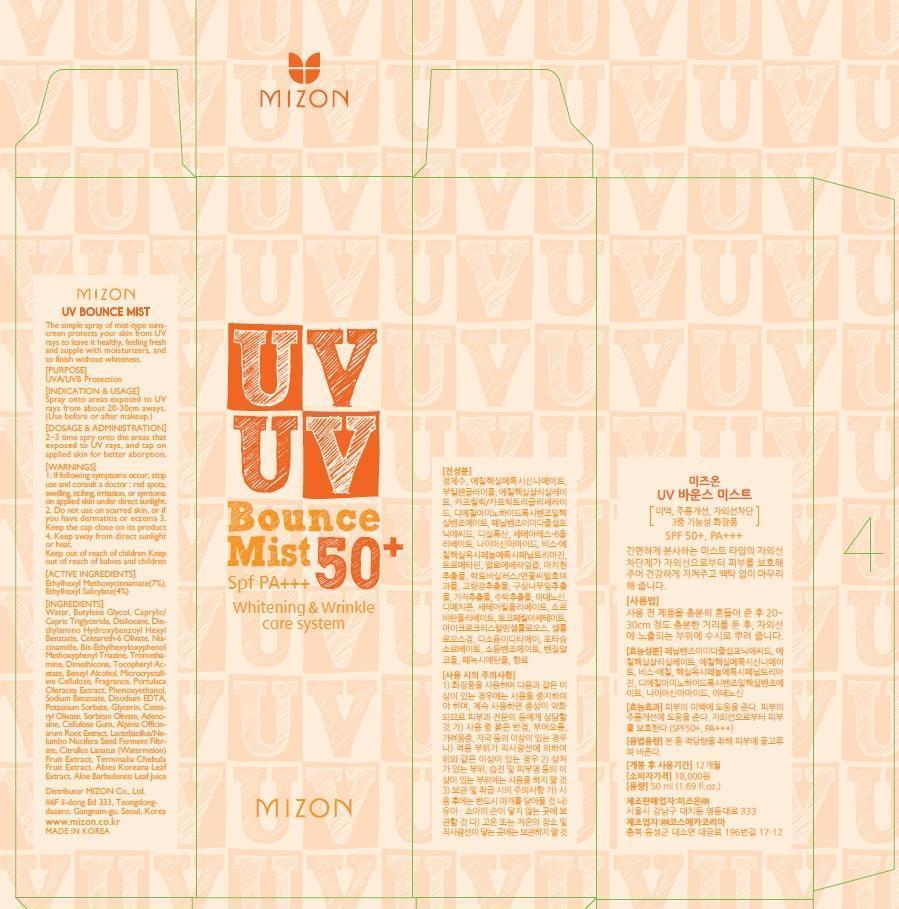 DRUG LABEL: UV BOUNCE MIST
NDC: 57718-030 | Form: SPRAY
Manufacturer: MIZON CO., LTD.
Category: otc | Type: HUMAN OTC DRUG LABEL
Date: 20140417

ACTIVE INGREDIENTS: OCTINOXATE 3.5 mg/50 mL; OCTISALATE 2 mg/50 mL
INACTIVE INGREDIENTS: Water; Butylene Glycol

ACTIVE INGREDIENT

Active Ingredients: Ethylhexyl Methoxycinnamate 7%, Ethylhexyl Salicylate 4%

INACTIVE INGREDIENT

Inactive Ingredients:
Water, Butylene Glycol, Caprylic/Capric Triglyceride, Phenylbenzimidazole Sulfonic Acid, Disiloxane, Diethylamino Hydroxybenzoyl Hexyl Benzoate, Ceteareth-6 Olivate, Niacinamide, Bis-Ethylhexyloxyphenol Methoxyphenyl Triazine, Tromethamine, Dimethicone, Tocopheryl Acetate, Benzyl Alcohol, Microcrystalline Cellulose, Fragrance, Portulaca Oleracea Extract, Phenoxyethanol, Sodium Benzoate, Disodium EDTA, Potassium Sorbate, Glycerin, Cetearyl Olivate, Sorbitan Olivate, Adenosine, Cellulose Gum, Alpinia Officinarum Root Extract, Lactobacillus/Nelumbo Nucifera Seed Ferment Filtrate, Citrullus Lanatus (Watermelon) Fruit Extract, Terminalia Chebula Fruit Extract, Abies Koreana Leaf Extract, Aloe Barbadensis Leaf Juice

PURPOSE

Purpose: UVA/UVB Protection

WARNINGS

1. If following symptoms occur, stop use and consult a doctor: red spots, swelling, itcihng, irritation, or symtoms on applied skin under direct sunlight.
2. Do not use on scarred skin, or if you have dermatitis or eczema
3. Keep the cap close on its product
4. Keep away from direct sunlight or heat.

KEEP OUT OF REACH OF CHILDREN

Keep out of reach of babies and children

INDICATIONS AND USAGE

Indication and Usage:
Spray onto areas exposed to UV rays from about 20-30cm aways. (Use before or after makeup.)

DOSAGE AND ADMINISTRATION

2-3 time spry onto the areas that exposed to UV rays, and tap on applied skin for better aborption.